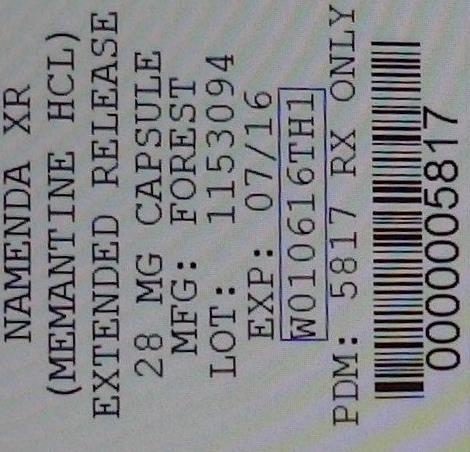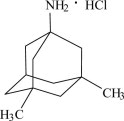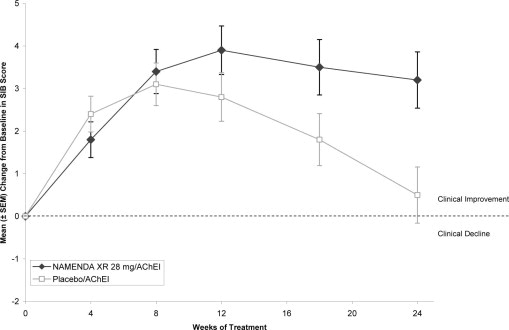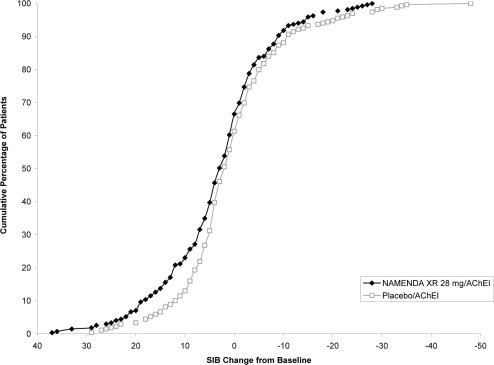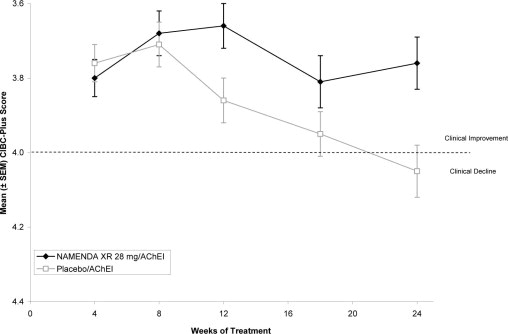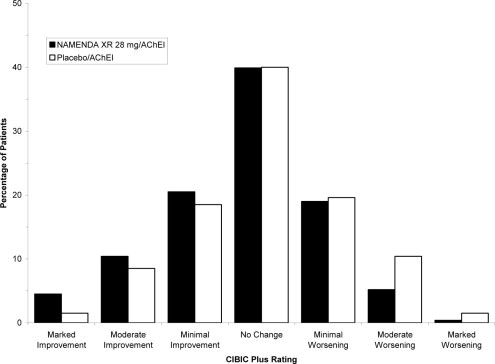 DRUG LABEL: Namenda
                                    
NDC: 68151-5817 | Form: CAPSULE, EXTENDED RELEASE
Manufacturer: Carilion Materials Management
Category: prescription | Type: HUMAN PRESCRIPTION DRUG LABEL
Date: 20140716

ACTIVE INGREDIENTS: MEMANTINE HYDROCHLORIDE 28 mg/1 1
INACTIVE INGREDIENTS: sucrose; povidone K30; hypromellose 2910 (15 MPA.S); talc; polyethylene glycol 400; POLYETHYLENE GLYCOL 8000; ETHYLCELLULOSE (100 MPA.S); AMMONIA

HIGHLIGHTS OF PRESCRIBING INFORMATION

These highlights do not include all the information needed to use NAMENDA XR capsules safely and effectively. See full prescribing information for NAMENDA XR capsules. NAMENDA XR (memantine hydrochloride) extended release capsules Initial U.S. Approval: 2003
®

1 INDICATIONS AND USAGE

NAMENDA XR contains memantine HCl, an NMDA receptor antagonist indicated for the treatment of moderate to severe dementia of the Alzheimer's type. () 1

2 DOSAGE AND ADMINISTRATION

Initial Dose 7 mg NAMENDA XR once daily () 2.1

Maintenance Dose 28 mg NAMENDA XR once daily () 2.1

A minimum of 1 week of treatment with the previous dose should be observed before increasing the dose. () 2.1

A target dose of 14 mg once daily is recommended in patients with severe renal impairment. () 2.1

3 DOSAGE FORMS AND STRENGTHS

NAMENDA XR is available as an extended-release capsule () in the following strengths: 7 mg, 14 mg, 21 mg, 28 mg (,) 3.13.13.2

4 CONTRAINDICATIONS

NAMENDA XR is contraindicated in patients with known hypersensitivity to memantine hydrochloride or to any excipients used in the formulation. () 4.1

5 WARNINGS AND PRECAUTIONS

Conditions that raise urine pH may decrease the urinary elimination of memantine resulting in increased plasma levels of memantine. () 5.1

6 ADVERSE REACTIONS

The most commonly observed adverse reactions occurring at a frequency of at least 5% and greater than placebo with administration of NAMENDA XR 28 mg/day were headache, diarrhea and dizziness. Other less common and sometimes serious adverse events have been reported. () 6

. To report SUSPECTED ADVERSE REACTIONS, Contact Forest Laboratories, Inc. at 1-800-678-1605 or FDA at 1-800-FDA-1088 or www.fda.gov/medwatch

7 DRUG INTERACTIONS

Use with other NMDA antagonists (amantadine, ketamine, and dextromethorphan) has not been systematically evaluated and such use should be approached with caution. () 7.1

8. USE IN SPECIFIC POPULATIONS

Pediatric Use: The safety and effectiveness of NAMENDA XR in pediatric patients have not been established. () 8.4

FULL PRESCRIBING INFORMATION

1 INDICATIONS AND USAGE

NAMENDA XR (memantine hydrochloride) extended-release capsules are indicated for the treatment of moderate to severe dementia of the Alzheimer's type.

2 DOSAGE AND ADMINISTRATION

2.1 Recommended Dosing

The dosage of NAMENDA XR shown to be effective in a controlled clinical trial is 28 mg once daily.

The recommended starting dose of NAMENDA XR is 7 mg once daily. The recommended target dose is 28 mg once daily. The dose should be increased in 7 mg increments to 28 mg once daily. The minimum recommended interval between dose increases is one week, and only if the previous dose has been well tolerated. The maximum recommended dose is 28 mg once daily.

NAMENDA XR can be taken with or without food. NAMENDA XR capsules can be taken intact or may be opened, sprinkled on applesauce, and thereby swallowed. The entire contents of each NAMENDA XR capsule should be consumed; the dose should not be divided.

Except when opened and sprinkled on applesauce, as described above, NAMENDA XR should be swallowed whole. NAMENDA XR capsules should not be divided, chewed, or crushed.

Switching from NAMENDA Tablets to NAMENDA XR Capsules:

Patients treated with NAMENDA tablets may be switched to NAMENDA XR capsules as follows:

It is recommended that a patient who is on a regimen of 10 mg twice daily of NAMENDA tablets be switched to NAMENDA XR 28 mg once daily capsules the day following the last dose of a 10 mg NAMENDA tablet. There is no study addressing the comparative efficacy of these 2 regimens.

In a patient with severe renal impairment, it is recommended that a patient who is on a regimen of 5 mg twice daily of NAMENDA tablets be switched to NAMENDA XR 14 mg once daily capsules the day following the last dose of a 5 mg NAMENDA tablet.

Special Populations:

Hepatic Impairment

No dosage adjustment is recommended in patients with mild or moderate hepatic impairment. NAMENDA XR should be administered with caution to patients with severe hepatic impairment.

Renal Impairment

No dosage adjustment is recommended in patients with mild or moderate renal impairment.

A target dose of 14 mg/day is recommended in patients with severe renal impairment (creatinine clearance of 5 – 29 mL/min, based on the Cockroft-Gault equation).

3 DOSAGE FORMS AND STRENGTHS

3.1 Dosage Form

Capsule:

Each capsule contains 7 mg, 14 mg, 21 mg or 28 mg of memantine HCl.

The 7 mg capsules are a yellow opaque #4 size capsule, with “FLI 7 mg” black imprint.

The 14 mg capsules are a yellow cap and dark green opaque body #4 size capsule, with “FLI 14 mg” black imprint on the yellow cap.

The 21 mg capsules are a white to off-white cap and dark green opaque body #4 size capsule, with “FLI 21 mg” black imprint on the white to off-white cap.

The 28 mg capsules are a dark green opaque #3 size capsule, with “FLI 28 mg” white imprint.

3.2 Dosage Strengths

- Each 7 mg capsule contains 7 mg memantine HCl.
- Each 14 mg capsule contains 14 mg memantine HCl.
- Each 21 mg capsule contains 21 mg memantine HCl.
- Each 28 mg capsule contains 28 mg memantine HCl.

For a full list of excipients, see . Description () 11

4 CONTRAINDICATIONS

4.1 Hypersensitivity

NAMENDA XR is contraindicated in patients with known hypersensitivity to memantine hydrochloride or to any excipients used in the formulation See . [Description ()] 11

5 WARNINGS AND PRECAUTIONS

5.1 Genitourinary Conditions

Conditions that raise urine pH may decrease the urinary elimination of memantine resulting in increased plasma levels of memantine.

5.2 Seizures

NAMENDA XR has not been systematically evaluated in patients with a seizure disorder. In clinical trials of memantine, seizures occurred in 0.3% of patients treated with memantine and 0.6% of patients treated with placebo.

6 ADVERSE REACTIONS

6.1 Clinical Trial Data Sources

NAMENDA XR was evaluated in a double-blind placebo-controlled trial treating a total of 676 patients with moderate to severe dementia of the Alzheimer's type (341 patients treated with NAMENDA XR 28 mg/day dose and 335 patients treated with placebo) for a treatment period up to 24 weeks.

Because clinical trials are conducted under widely varying conditions, adverse reaction rates observed in the clinical trials of a drug cannot be directly compared to rates in the clinical trials of another drug and may not reflect the rates observed in practice.

6.2 Adverse Reactions Leading to Discontinuation

In the placebo-controlled clinical trial of NAMENDA XR [See)], which treated a total of 676 patients, the proportion of patients in the NAMENDA XR 28 mg/day dose and placebo groups who discontinued treatment due to adverse events were 10.0% and 6.3%, respectively. The most common adverse reaction in the NAMENDA XR treated group that led to treatment discontinuation in this study was dizziness at a rate of 1.5%. Clinical Studies (14

6.3 Most Common Adverse Reactions

The most commonly observed adverse reactions seen in patients administered NAMENDA XR in the controlled clinical trial, defined as those occurring at a frequency of at least 5% in the NAMENDA XR group and at a higher frequency than placebo were headache, diarrhea and dizziness.

lists treatment-emergent adverse reactions that were observed at an incidence of ≥ 2% in the NAMENDA XR treated group and occurred at a rate greater than placebo. Table 1

Table 1: Adverse reactions observed with a frequency of ≥ 2% and occurring with a rate greater than placebo
Adverse reaction | Placebo (n = 335) % | NAMENDA XR 28mg (n = 341) %
Gastrointestinal Disorders
Diarrhea | 4 | 5
Constipation | 1 | 3
Abdominal pain | 1 | 2
Vomiting | 1 | 2
Infections and infestations
Influenza | 3 | 4
Investigations
Weight, increased | 1 | 3
Musculoskeletal and connective tissue disorders
Back pain | 1 | 3
Nervous system disorders
Headache | 5 | 6
Dizziness | 1 | 5
Somnolence | 1 | 3
Psychiatric disorders
Anxiety | 3 | 4
Depression | 1 | 3
Aggression | 1 | 2
Renal and urinary disorders
Urinary incontinence | 1 | 2
Vascular disorders
Hypertension | 2 | 4
Hypotension | 1 | 2

6.4 Vital Sign Changes

NAMENDA XR and placebo groups were compared with respect to (1) mean change from baseline in vital signs (pulse, systolic blood pressure, diastolic blood pressure, and weight) and (2) the incidence of patients meeting criteria for potentially clinically significant changes from baseline in these variables. There were no clinically important changes in vital signs in patients treated with NAMENDA XR. A comparison of supine and standing vital sign measures for NAMENDA XR and placebo in Alzheimer's patients indicated that NAMENDA XR treatment is not associated with orthostatic changes.

6.5 Laboratory Changes

NAMENDA XR and placebo groups were compared with respect to (1) mean change from baseline in various serum chemistry, hematology, and urinalysis variables and (2) the incidence of patients meeting criteria for potentially clinically significant changes from baseline in these variables. These analyses revealed no clinically important changes in laboratory test parameters associated with NAMENDA XR treatment.

6.6 ECG Changes

NAMENDA XR and placebo groups were compared with respect to (1) mean change from baseline in various ECG parameters and (2) the incidence of patients meeting criteria for potentially clinically significant changes from baseline in these variables. These analyses revealed no clinically important changes in ECG parameters associated with NAMENDA XR treatment.

6.7 Other Adverse Reactions Observed During Clinical Trials of NAMENDA XR

Following is a list of treatment-emergent adverse reactions reported from 750 patients treated with NAMENDA XR for periods up to 52 weeks in double-blind or open-label clinical trials. The listing does not include those events already listed in , those events for which a drug cause was remote, those events for which descriptive terms were so lacking in specificity as to be uninformative, and those events reported only once which did not have a substantial probability of being immediately life threatening. Events are categorized by body system. Table 1

anemia. Blood and Lymphatic System Disorders:

bradycardia, myocardial infarction. Cardiac Disorders:

fecal incontinence, nausea. Gastrointestinal Disorders:

asthenia, fatigue, gait disturbance, irritability, peripheral edema, pyrexia. General Disorders:

bronchitis, nasopharyngitis, pneumonia, upper respiratory tract infection, urinary tract infection. Infections and Infestations:

fall. Injury, Poisoning and Procedural Complications:

weight decreased. Investigations:

anorexia, dehydration, decreased appetite, hyperglycemia. Metabolism and Nutrition Disorders:

arthralgia, pain in extremity. Musculoskeletal and Connective Tissue Disorders:

convulsion, dementia Alzheimer's type, syncope, tremor. Nervous System Disorders:

agitation, confusional state, delirium, delusion, disorientation, hallucination, insomnia, restlessness. Psychiatric Disorders:

cough, dyspnea. Respiratory, Thoracic and Mediastinal Disorders:

6.8 Memantine Immediate Release Clinical Trial and Post Marketing Spontaneous Reports

The following additional adverse reactions have been identified from previous worldwide experience with memantine (immediate release) use. These adverse reactions have been chosen for inclusion because of a combination of seriousness, frequency of reporting, or potential causal connection to memantine and have not been listed elsewhere in labeling. However, because some of these adverse reactions were reported voluntarily from a population of uncertain size, it is not always possible to reliably estimate their frequency or establish a causal relationship between their occurrence and the administration of memantine. These events include:

agranulocytosis, leukopenia (including neutropenia), pancytopenia, thrombocytopenia. thrombotic thrombocytopenic purpura. Blood and Lymphatic System Disorders:

atrial fibrillation, atrioventricular block (including 2nd and 3rd degree block), cardiac failure, orthostatic hypotension, and torsades de pointes. Cardiac Disorders:

inappropriate antidiuretic hormone secretion. Endocrine Disorders:

colitis, pancreatitis. Gastrointestinal disorders:

malaise, sudden death. General disorders and administration site conditions:

hepatitis (including abnormal hepatic function test, cytolytic and cholestatic hepatitis), hepatic failure. Hepatobiliary Disorders:

sepsis. Infections and infestations:

electrocardiogram QT prolonged, international normalized ratio increased. Investigations:

hypoglycaemia, hyponatraemia. Metabolism and Nutrition Disorders:

convulsions (including grand mal), cerebrovascular accident, dyskinesia, extrapyramidal disorder, hypertonia, loss of consciousness, neuroleptic malignant syndrome, Parkinsonism, tardive dyskinesia, transient ischemic attack. Nervous System Disorders:

hallucinations (both visual and auditory), restlessness, suicidal ideation. Psychiatric Disorders:

acute renal failure (including abnormal renal function test), urinary retention. Renal and Urinary Disorders:

rash, Stevens Johnson syndrome. Skin Disorders:

pulmonary embolism, thrombophlebitis, deep venous thrombosis. Vascular Disorders:

The following adverse events have been reported to be temporally associated with memantine treatment and are not described elsewhere in the product labeling: aspiration pneumonia, bone fracture, carpal tunnel syndrome, cerebral infarction, chest pain, cholelithiasis, claudication, depressed level of consciousness (including rare reports of coma), dysphagia, encephalopathy, gastritis, gastroesophageal reflux, intracranial hemorrhage, hyperglycemia, hyperlipidemia, ileus, impotence, lethargy, myoclonus, supraventricular tachycardia, and tachycardia. However, there is again no evidence that any of these additional adverse events are caused by memantine.

7 DRUG INTERACTIONS

No drug-drug interaction studies have been conducted with NAMENDA XR, specifically.

7.1 Use with other N-methyl-D-aspartate (NMDA) Antagonists

The combined use of NAMENDA XR with other NMDA antagonists (amantadine, ketamine, and dextromethorphan) has not been systematically evaluated and such use should be approached with caution.

7.2 Effect of Memantine on the Metabolism of Other Drugs

studies conducted with marker substrates of CYP450 enzymes (CYP1A2, -2A6, -2C9, -2D6, -2E1, -3A4) showed minimal inhibition of these enzymes by memantine. In addition, i studies indicate that at concentrations exceeding those associated with efficacy, memantine does not induce the cytochrome P450 isozymes CYP1A2, -2C9, -2E1 and -3A4/5. No pharmacokinetic interactions with drugs metabolized by these enzymes are expected. In vitron vitro

Pharmacokinetic studies evaluated the potential of memantine for interaction with donepezil (See) and bupropion. Coadministration of memantine with the AChE inhibitor donepezil HCl does not affect the pharmacokinetics of either compound. Memantine did not affect the pharmacokinetics of the CYP2B6 substrate bupropion or its metabolite hydroxybupropion. Section Use with Cholinesterase Inhibitors 7.7

7.3 Effect of Other Drugs on Memantine

Memantine is predominantly renally eliminated, and drugs that are substrates and/or inhibitors of the CYP450 system are not expected to alter the pharmacokinetics of memantine. A clinical drug-drug interaction study indicated that bupropion did not affect the pharmacokinetics of memantine.

7.4 Drugs Eliminated via Renal Mechanisms

Because memantine is eliminated in part by tubular secretion, coadministration of drugs that use the same renal cationic system, including hydrochlorothiazide (HCTZ), triamterene (TA), metformin, cimetidine, ranitidine, quinidine, and nicotine, could potentially result in altered plasma levels of both agents. However, coadministration of memantine and HCTZ/TA did not affect the bioavailability of either memantine or TA, and the bioavailability of HCTZ decreased by 20%. In addition, coadministration of memantine with the antihyperglycemic drug Glucovance (glyburide and metformin HCl) did not affect the pharmacokinetics of memantine, metformin and glyburide. Furthermore, memantine did not modify the serum glucose lowering effect of Glucovance , indicating the absence of a pharmacodynamic interaction.®®

7.5 Drugs That Make the Urine Alkaline

The clearance of memantine was reduced by about 80% under alkaline urine conditions at pH 8. Therefore, alterations of urine pH towards the alkaline condition may lead to an accumulation of the drug with a possible increase in adverse effects. Urine pH is altered by diet, drugs (e.g. carbonic anhydrase inhibitors, sodium bicarbonate) and clinical state of the patient (e.g. renal tubular acidosis or severe infections of the urinary tract). Hence, memantine should be used with caution under these conditions.

7.6 Drugs Highly Bound to Plasma Proteins

Because the plasma protein binding of memantine is low (45%), an interaction with drugs that are highly bound to plasma proteins, such as warfarin and digoxin, is unlikely [see Section .] 7

7.7 Use with Cholinesterase Inhibitors

Coadministration of memantine with the AChE inhibitor donepezil HCl did not affect the pharmacokinetics of either compound. In a 24-week controlled clinical study in patients with moderate to severe Alzheimer's disease, the adverse event profile observed with a combination of memantine immediate-release and donepezil was similar to that of donepezil alone.

8. USE IN SPECIFIC POPULATIONS

8.1 Pregnancy

There are no adequate and well-controlled studies of NAMENDA XR in pregnant women. NAMENDA XR should be used during pregnancy only if the potential benefit justifies the potential risk to the fetus. Pregnancy Category B:

Memantine given orally to pregnant rats and pregnant rabbits during the period of organogenesis was not teratogenic up to the highest doses tested (18 mg/kg/day in rats and 30 mg/kg/day in rabbits, which are 6 and 21 times, respectively, the maximum recommended human dose [MRHD] on a mg/m basis).^2

Slight maternal toxicity, decreased pup weights and an increased incidence of non-ossified cervical vertebrae were seen at an oral dose of 18 mg/kg/day in a study in which rats were given oral memantine beginning pre-mating and continuing through the postpartum period. Slight maternal toxicity and decreased pup weights were also seen at this dose in a study in which rats were treated from day 15 of gestation through the post-partum period. The no-effect dose for these effects was 6 mg/kg, which is 2 times the MRHD on a mg/m basis.^2

8.3 Nursing Mothers

It is not known whether memantine is excreted in human milk. Because many drugs are excreted in human milk, caution should be exercised when memantine is administered to a nursing mother.

8.4 Pediatric Use

The safety and effectiveness of memantine in pediatric patients have not been established.

Memantine failed to demonstrate efficacy in two 12-week controlled clinical studies of 578 pediatric patients aged 6-12 years with autism spectrum disorders (ASD), including autism, Asperger's disorder, and Pervasive Development Disorder - Not Otherwise Specified (PDD-NOS). Memantine has not been studied in pediatric patients under 6 years of age or over 12 years of age. Memantine treatment was initiated at 3 mg/day and the dose was escalated to the target dose (weight-based) by week 6. Oral doses of memantine 3, 6, 9, or 15 mg extended-release capsules were administered once daily to patients with weights < 20 kg, 20-39 kg, 40-59 kg and ≥ 60 kg, respectively.

In a randomized, 12-week double-blind, placebo-controlled parallel study (Study A) in patients with autism, there was no statistically significant difference in the Social Responsiveness Scale (SRS) total raw score between patients randomized to memantine (n=54) and those randomized to placebo (n=53). In a 12-week responder-enriched randomized withdrawal study (Study B) in 471 patients with ASD, there was no statistically significant difference in the loss of therapeutic response rates between patients randomized to remain on full-dose memantine (n=153) and those randomized to switch to placebo (n=158).

The overall safety profile of memantine in pediatric patients was generally consistent with the known safety profile in adults [ ]. see Adverse Reactions (6.1)

In Study A, the treatment emergent adverse events in the memantine group (n=56) that were reported in at least 5% of patients and twice that in the placebo group (N=58) are listed in : Table 2

Table 2: Study A Commonly Reported Adverse Events With a Frequency ≥ 5% and Twice That in Placebo
Adverse Event | Memantine N=56 | Placebo N=58
Cough | 8.9% | 3.4%
Influenza | 7.1% | 3.4%
Rhinorrhea | 5.4% | 0%
Agitation | 5.4% | 1.7%
Discontinuations due to adverse eventsa
Aggression | 3.6% | 1.7%
Irritability | 1.8% | 3.4%
Reported adverse events leading to discontinuation in more than one patient in either treatment group.a

The treatment emergent adverse events that were reported in at least 5% of patients in the 12-48 week open-label study to identify responders to enroll in Study B are listed in : Table 3

Table 3: 12-48 Week Open Label Lead-In study to Study B Commonly Reported Adverse Events With a Frequency ≥ 5%
Adverse Event | Memantine N=903
Headache | 8.0%
Nasopharyngitis | 6.3%
Pyrexia | 5.8%
Irritability | 5.4%
Discontinuations due to adverse eventsa
Irritability | 1.2%
Aggression | 1.0%
At least 1% incidence of adverse events leading to premature discontinuation.a

In the randomized withdrawal study (Study B), the treatment emergent adverse event in patients randomized to placebo (n=160) and reported in at least 5% of patients and twice that of the full-dose memantine treatment group (n=157) was irritability (5.0% vs 2.5%).

In a juvenile animal study, male and female juvenile rats were administered memantine (15, 30, and 45 mg/kg/day) starting on postnatal day (PND) 14 through PND 70. Body weights were reduced at 45 mg/kg/day. Delays in sexual maturation were noted in male and female rats at doses ≥ 30 mg/kg/day. Memantine induced neuronal lesions in several areas of the brain on PND 15 and 17 at doses ≥ 30 mg/kg/day. Behavioral toxicity (decrease percent of auditory startle habituation) was noted for animals in the 45 mg/kg/day dose group. The 15 mg/kg/day dose was considered the No-Observed-Adverse-Effect-Level (NOAEL) for this study.

In a second juvenile rat toxicity study, male and female juvenile rats were administered memantine (1, 3, 8, 15, 30, and 45 mg/kg/day) starting on postnatal day (PND) 7 through PND 70. Due to early memantine-related mortality, the 30 and 45 mg/kg/day dose groups were terminated without further evaluation. Memantine induced apoptosis or neuronal degeneration in several areas of the brain on PND 8, 10, and 17 at a dose of 15 mg/kg/day. The NOAEL for apoptosis and neuronal degeneration was 8 mg/kg/day. Behavioral toxicity (effects on motor activity, auditory startle habituation, and learning and memory) was noted at doses ≥ 3 mg/kg/day during treatment, but was not seen after drug discontinuation. Therefore, the 1 mg/kg/day dose was considered the NOAEL for the neurobehavioral effect in this study.

9 DRUG ABUSE AND DEPENDENCE

Memantine is not a controlled substance. Memantine is a low to moderate affinity uncompetitive NMDA antagonist that did not produce any evidence of drug-seeking behavior or withdrawal symptoms upon discontinuation in 3,254 patients who participated in clinical trials at therapeutic doses. Post marketing data, outside the U.S., retrospectively collected, has provided no evidence of drug abuse or dependence.

10 OVERDOSAGE

Signs and symptoms most often accompanying overdosage with other formulations of memantine in clinical trials and from worldwide marketing experience, alone or in combination with other drugs and/or alcohol, include agitation, asthenia, bradycardia, confusion, coma, dizziness, ECG changes, increased blood pressure, lethargy, loss of consciousness, psychosis, restlessness, slowed movement, somnolence, stupor, unsteady gait, visual hallucinations, vertigo, vomiting, and weakness. The largest known ingestion of memantine worldwide was 2 grams in an individual who took memantine in conjunction with unspecified antidiabetic medications. This person experienced coma, diplopia, and agitation, but subsequently recovered.

One patient participating in a NAMENDA XR clinical trial unintentionally took 112 mg of NAMENDA XR daily for 31 days and experienced an elevated serum uric acid, elevated serum alkaline phosphatase, and low platelet count.

No fatalities have been noted with overdoses of memantine alone. A fatal outcome has very rarely been reported when memantine has been ingested as part of overdosing with multiple drugs; in those instances, the relationship between memantine and a fatal outcome has been unclear.

Because strategies for the management of overdose are continually evolving, it is advisable to contact a poison control center to determine the latest recommendations for the management of an overdose of any drug. As in any cases of overdose, general supportive measures should be utilized, and treatment should be symptomatic. Elimination of memantine can be enhanced by acidification of urine.

11 DESCRIPTION

NAMENDA XR is an orally active NMDA receptor antagonist. The chemical name for memantine hydrochloride is 1-amino-3,5-dimethyladamantane hydrochloride with the following structural formula:

The molecular formula is C H N•HCl and the molecular weight is 215.76. Memantine HCl occurs as a fine white to off-white powder and is soluble in water.1221

NAMENDA XR capsules are supplied for oral administration as 7, 14, 21 and 28 mg capsules (see Section). Each capsule contains extended release beads with the labeled amount of memantine HCl and the following inactive ingredients: sugar spheres, polyvinylpyrrolidone, hypromellose, talc, polyethylene glycol, ethylcellulose, ammonium hydroxide, oleic acid, and medium chain triglycerides in hard gelatin capsules. How Supplied 16

12 CLINICAL PHARMACOLOGY

12.1 Mechanism of Action

Persistent activation of central nervous system N-methyl-D-aspartate (NMDA) receptors by the excitatory amino acid glutamate has been hypothesized to contribute to the symptomatology of Alzheimer's disease. Memantine is postulated to exert its therapeutic effect through its action as a low to moderate affinity uncompetitive (open-channel) NMDA receptor antagonist which binds preferentially to the NMDA receptor-operated cation channels. There is no evidence that memantine prevents or slows neurodegeneration in patients with Alzheimer's disease.

12.2 Pharmacodynamics

Memantine showed low to negligible affinity for GABA, benzodiazepine, dopamine, adrenergic, histamine and glycine receptors and for voltage-dependent Ca , Na or K channels. Memantine also showed antagonistic effects at the 5HT receptor with a potency similar to that for the NMDA receptor and blocked nicotinic acetylcholine receptors with one-sixth to one-tenth the potency.^2+^+^+3

studies have shown that memantine does not affect the reversible inhibition of acetylcholinesterase by donepezil, galantamine, or tacrine. In vitro

12.3 Pharmacokinetics

Memantine is well absorbed after oral administration and has linear pharmacokinetics over the therapeutic dose range. It is excreted predominantly unchanged in urine and has a terminal elimination half-life of about 60-80 hours. In a study comparing 28 mg once daily NAMENDA XR to 10 mg twice daily NAMENDA C and AUC values were 48% and 33% higher for the XR dosage regimen, respectively.max0-24

Absorption

After multiple dose administration of NAMENDA XR, memantine peak concentrations occur around 9-12 hours postdose. There is no difference in the absorption of NAMENDA XR when the capsule is taken intact or when the contents are sprinkled on applesauce.

There is no difference in memantine exposure, based on C or AUC, for NAMENDA XR whether that drug product is administered with food or on an empty stomach. However, peak plasma concentrations are achieved about 18 hours after administration with food versus approximately 25 hours after administration on an empty stomach.max

Distribution

The mean volume of distribution of memantine is 9-11 L/kg and the plasma protein binding is low (45%).

Metabolism

Memantine undergoes partial hepatic metabolism. The hepatic microsomal CYP450 enzyme system does not play a significant role in the metabolism of memantine.

Elimination

Memantine is excreted predominantly in the urine, unchanged, and has a terminal elimination half-life of about 60-80 hours. About 48% of administered drug is excreted unchanged in urine; the remainder is converted primarily to three polar metabolites which possess minimal NMDA receptor antagonistic activity: the N-glucuronide conjugate, 6-hydroxy memantine, and 1-nitroso-deaminated memantine. A total of 74% of the administered dose is excreted as the sum of the parent drug and the N-glucuronide conjugate. Renal clearance involves active tubular secretion moderated by pH dependent tubular reabsorption.

12.4 Pharmacokinetics in Special Populations

Hepatic Impairment

Memantine pharmacokinetics were evaluated following the administration of single oral doses of 20 mg in 8 subjects with moderate hepatic impairment (Child-Pugh Class B,score 7-9) and 8 subjects who were age-, gender-, and weight-matched to the hepatically-impaired subjects. There was no change in memantine exposure (based on Cmax and AUC) in subjects with moderate hepatic impairment as compared with healthy subjects. However, terminal elimination half-life increased by about 16% in subjects with moderate hepatic impairment as compared with healthy subjects. No dose adjustment is recommended for patients with mild and moderate hepatic impairment. NAMENDA XR should be administered with caution to patients with severe hepatic impairment as the pharmacokinetics of memantine have not been evaluated in that population.

Renal Impairment

Memantine pharmacokinetics were evaluated following single oral administration of 20 mg memantine HCl in 8 subjects with mild renal impairment (creatinine clearance, CLcr, > 50 – 80 mL/min), 8 subjects with moderate renal impairment (CLcr 30 – 49 mL/min), 7 subjects with severe renal impairment (CLcr 5 – 29 mL/min) and 8 healthy subjects (CLcr > 80 mL/min) matched as closely as possible by age, weight and gender to the subjects with renal impairment. Mean AUC increased by 4%, 60%, and 115% in subjects with mild, moderate, and severe renal impairment, respectively, compared to healthy subjects. The terminal elimination half-life increased by 18%, 41%, and 95% in subjects with mild, moderate, and severe renal impairment, respectively, compared to healthy subjects.0-∞

No dosage adjustment is recommended for patients with mild and moderate renal impairment. Dosage should be reduced in patients with severe renal impairment See . [Dosage and Administration ()] 2

Gender

Following multiple dose administration of memantine HCl 20 mg daily, females had about 45% higher exposure than males, but there was no difference in exposure when body weight was taken into account.

Elderly

The pharmacokinetics of memantine in young and elderly subjects are similar.

13 NONCLINICAL TOXICOLOGY

13.1 Carcinogenesis, Mutagenesis, Impairment of Fertility

There was no evidence of carcinogenicity in a 113-week oral study in mice at doses up to 40 mg/kg/day (7 times the maximum recommended human dose [MRHD] on a mg/m basis). There was also no evidence of carcinogenicity in rats orally dosed at up to 40 mg/kg/day for 71 weeks followed by 20 mg/kg/day (14 and 7 times the MRHD on a mg/m basis, respectively) through 128 weeks.^2^2

Memantine produced no evidence of genotoxic potential when evaluated in the or reverse mutation assay, an chromosomal aberration test in human lymphocytes, an cytogenetics assay for chromosome damage in rats, and the mouse micronucleus assay. The results were equivocal in an gene mutation assay using Chinese hamster V79 cells. in vitro S. typhimurium E. coliin vitroin vivoin vivoin vitro

No impairment of fertility or reproductive performance was seen in rats administered up to 18 mg/kg/day (6 times the MRHD on a mg/m basis) orally from 14 days prior to mating through gestation and lactation in females, or for 60 days prior to mating in males.^2

13.2 Animal Toxicology

Memantine induced neuronal lesions (vacuolation and necrosis) in the multipolar and pyramidal cells in cortical layers III and IV of the posterior cingulate and retrosplenial neocortices in rats, similar to those which are known to occur in rodents administered other NMDA receptor antagonists. Lesions were seen after a single dose of memantine. In a study in which rats were given daily oral doses of memantine for 14 days, the no-effect dose for neuronal necrosis was 4 times the maximum recommended human dose (MRHD of 28 mg/day) on a mg/m basis.^2

In a neurotoxicity study, female rats were given oral doses of memantine (3, 10, 30, 60 mg/kg/day) alone or in combination with donepezil (3, 10 mg/kg/day) for 28 days. When administered alone, memantine induced neurodegeneration only at 60 mg/kg/day; however, when administered in combination with 10 mg/kg/day donepezil, memantine induced neurodegeneration at doses of 30 and 60 mg/kg/day. When 60 mg/kg/day memantine and 10 mg/kg/day donepezil were administered in combination, the incidence and severity of neurodegeneration was increased compared to that with 60 mg/kg/day memantine alone or with 30 mg/kg/day memantine in combination with 10 mg/kg/day donepezil. In addition, the combination of 60 mg/kg/day memantine and 10 mg/kg/day donepezil was associated with widespread neurodegeneration in cortical areas (perirhinal, temporal, entorhinal, frontal, insular, piriform) and in olfactory nucleus and subiculum, whereas in the other affected groups, there was limited cortical (entorhinal, retrosplenial) involvement. At the no-effect level of the combination (10 mg/kg/day memantine + 10 mg/kg/day donepezil), plasma exposures of memantine were similar to (AUC) or two times (Cmax) those expected in humans at the MRHD; plasma exposures of donepezil were 3 (AUC) or 6 (Cmax) times those in humans at the MRHD of donepezil (10 mg/day). In a published study, similar donepezil-mediated exacerbation of memantine-induced neurodegeneration was observed in female rats given single doses of memantine in combination with donepezil, both administered by intraperitoneal injection.

The potential for induction of central neurodegenerative lesions by NMDA receptor antagonists in humans is unknown.

14 CLINICAL STUDIES

The effectiveness of NAMENDA XR as a treatment for patients with moderate to severe Alzheimer's disease was based on the results of a double-blind, placebo-controlled trial.

24-week Study of NAMENDA XR Capsules

This was a randomized double-blind clinical investigation in outpatients with moderate to severe Alzheimer's disease (diagnosed by DSM-IV criteria and NINCDS-ADRDA criteria for AD with a Mini Mental State Examination (MMSE) score ≥ 3 and ≤ 14 at Screening and Baseline) receiving acetylcholinesterase inhibitor (AChEI) therapy at a stable dose for 3 months prior to screening. The mean age of patients participating in this trial was 76.5 years with a range of 49-97 years. Approximately 72% of patients were female and 94% were Caucasian.

Study Outcome Measures

The effectiveness of NAMENDA XR was evaluated in this study using the co-primary efficacy parameters of Severe Impairment Battery (SIB) and the Clinician's Interview-Based Impression of Change (CIBIC-Plus).

The ability of NAMENDA XR to improve cognitive performance was assessed with the Severe Impairment Battery (SIB), a multi-item instrument that has been validated for the evaluation of cognitive function in patients with moderate to severe dementia. The SIB examines selected aspects of cognitive performance, including elements of attention, orientation, language, memory, visuospatial ability, construction, praxis, and social interaction. The SIB scoring range is from 0 to 100, with lower scores indicating greater cognitive impairment.

The ability of NAMENDA XR to produce an overall clinical effect was assessed using a Clinician's Interview Based Impression of Change that required the use of caregiver information, the CIBIC-Plus. The CIBIC-Plus is not a single instrument and is not a standardized instrument like the ADCS-ADL or SIB. Clinical trials for investigational drugs have used a variety of CIBIC formats, each different in terms of depth and structure. As such, results from a CIBIC-Plus reflect clinical experience from the trial or trials in which it was used and cannot be compared directly with the results of CIBIC-Plus evaluations from other clinical trials. The CIBIC-Plus used in this trial was a structured instrument based on a comprehensive evaluation at baseline and subsequent time-points of four domains: general (overall clinical status), functional (including activities of daily living), cognitive, and behavioral. It represents the assessment of a skilled clinician using validated scales based on his/her observation during an interview with the patient, in combination with information supplied by a caregiver familiar with the behavior of the patient over the interval rated. The CIBIC-Plus is scored as a seven point categorical rating, ranging from a score of 1, indicating “marked improvement” to a score of 4, indicating “no change” to a score of 7, indicating “marked worsening.” The CIBIC-Plus has not been systematically compared directly to assessments not using information from caregivers (CIBIC) or other global methods.

Study Results

In this study, 677 patients were randomized to one of the following 2 treatments: NAMENDA XR 28 mg/day or placebo while still receiving an AChEI (either donepezil, galantamine, or rivastigmine).

Effects on Severe Impairment Battery (SIB)

shows the time course for the change from baseline in SIB score for the two treatment groups completing the 24 weeks of the study. At 24 weeks of treatment, the mean difference in the SIB change scores for the NAMENDA XR 28 mg/AChEI-treated (combination therapy) patients compared to the patients on placebo/AChEI (monotherapy) was 2.6 units. Using an LOCF analysis, NAMENDA XR 28 mg/AChEI treatment was statistically significantly superior to placebo/AChEI. Figure 1

Figure 1: Time course of the change from baseline in SIB score for patients completing 24 weeks of treatment.

shows the cumulative percentages of patients from each treatment group who had attained at least the measure of improvement in SIB score shown on the X axis. The curves show that both patients assigned to NAMENDA XR 28 mg/AChEI and placebo/AChEI have a wide range of responses, but that the NAMENDA XR 28 mg/AChEI group is more likely to show an improvement or a smaller decline. Figure 2

Figure 2: Cumulative percentage of patients completing 24 weeks of double-blind treatment with specified changes from baseline in SIB scores.

shows the time course for the CIBIC-Plus score for patients in the two treatment groups completing the 24 weeks of the study. At 24 weeks of treatment, the mean difference in the CIBIC-Plus scores for the NAMENDA XR 28 mg/AChEI-treated patients compared to the patients on placebo/AChEI was 0.3 units. Using an LOCF analysis, NAMENDA XR 28 mg/AChEI treatment was statistically significantly superior to placebo/AChEI. Figure 3

Figure 3: Time course of the CIBIC-Plus score for patients completing 24 weeks of treatment.

is a histogram of the percentage distribution of CIBIC-Plus scores attained by patients assigned to each of the treatment groups who completed 24 weeks of treatment. Figure 4

Figure 4: Distribution of CIBIC-Plus ratings at week 24

16 HOW SUPPLIED/STORAGE AND HANDLING

NDC:68151-5817-8 in a CUP of 1 CAPSULE, EXTENDED RELEASES

Storage

Store at 25°C (77°F); excursions permitted to 15-30°C (59-86°F) [see USP Controlled Room Temperature].

17 PATIENT COUNSELING INFORMATION

See FDA-approved patient labeling.

To assure safe and effective use of NAMENDA XR, the information and instructions provided in the patient information section should be discussed with patients and caregivers.

Patients and caregivers should be instructed to take NAMENDA XR only once per day, as prescribed.

Patients and caregivers should be instructed that NAMENDA XR capsules be swallowed whole. Alternatively, NAMENDA XR capsules may be opened and sprinkled on applesauce and the entire contents should be consumed. The capsules should not be divided, chewed or crushed.

Patients and caregivers should be advised that the product may cause headache, diarrhea and dizziness.

Manufactured for:Forest Pharmaceuticals, Inc. Subsidiary of Forest Laboratories, Inc. St. Louis, MO 63045

Manufactured by: Forest Laboratories Ireland Ltd

Licensed from Merz Pharmaceuticals GmbH

PATIENT INFORMATION

NAMENDA XR [Nuh-MEN-dah Eks-Are]

(memantine hydrochloride) Extended Release Capsules

What is NAMENDA XR and what is it used for?

NAMENDA XR belongs to a class of substances called NMDA antagonists. It is used for the treatment of patients with Alzheimer's disease.

Do not take NAMENDA XR in the following cases:

If you know that you are allergic (hyper-sensitive) to memantine (the active substance in NAMENDA XR) or to any of the other ingredients of NAMENDA XR [see ]. Description () 11

Take special care with NAMENDA XR if:

- You have, or ever had seizures.
- You have, or ever had difficulty passing urine.

If any of these apply to you, your doctor may need to monitor you more closely while you are on this medicine.

NAMENDA XR with food and drink:

NAMENDA XR may be taken with or without food. NAMENDA XR capsules may be opened and sprinkled on applesauce before swallowing, but the contents of the entire capsule should be taken and the dose should not be divided. Except when opened and sprinkled on applesauce, NAMENDA XR capsules must be swallowed whole and never crushed, divided or chewed [see ]. Dosage and Administration () 2

NAMENDA XR and older people:

NAMENDA XR can be used by patients over the age of 65, as well as by patients with Alzheimer's Disease who are aged 65 years or younger.

NAMENDA XR and children:

The use of NAMENDA XR in children is not recommended.

Pregnant women:

Tell your doctor if you are pregnant or planning to become pregnant. In the event of pregnancy, the benefits of NAMENDA XR must be assessed against the possible effects on your unborn child. Ask your doctor or pharmacist for advice before taking any medicine during pregnancy.

Breast-feeding mothers:

You should not breast-feed during treatment with NAMENDA XR. Ask your doctor or pharmacist for advice before taking any medicine while you are breast-feeding.

Taking other medicines:

Tell your doctor or pharmacist about any other medicines you are taking or have recently taken, including any you have taken without a prescription.

How to use NAMENDA XR:

Follow all instructions given to you by your doctor carefully, even if they differ from the ones given in this leaflet.

How to start treatment:

Treatment begins at a low dose (7 mg, once a day) and is gradually increased until the target dose (28 mg, once a day) is reached. To be effective, NAMENDA XR must be taken correctly, according to the following schedule:

Week 1: Start on Day 1

Take one 7 mg capsule each day.

Week 2: Start on Day 8

Take one 14 mg capsule each day.

Week 3: Start on Day 15

Take one 21 mg capsule each day.

Week 4: Start on Day 22

Take one 28 mg capsule each day.

Once the target dose (28 mg, once a day) has been reached, you can continue with that daily schedule unless told otherwise by your healthcare professional. (For patients with severe renal impairment, 14 mg once a day is the recommended dose.)

During the course of treatment, your healthcare professional may change the dose to suit your individual needs.

If you are currently taking another formulation of memantine, talk to your healthcare professional about how to switch to NAMENDA XR.

What to do if you take more NAMENDA XR capsules than you should:

If you accidentally take more NAMENDA XR capsules than you should, inform your healthcare professional that you have accidentally taken more NAMENDA XR than you should have. You may require medical attention. Some people who have accidentally taken too much memantine have experienced dizziness, unsteadiness, weakness, tiredness, confusion, as well as other symptoms.

If you forget to take NAMENDA XR:

If you forget to take one dose of NAMENDA XR, do not double-up on your next dose. Take only your next dose as scheduled.

If you have forgotten to take NAMENDA XR for several days, do not take the next dose until you have talked to your healthcare professional.

Possible side effects:

Like all medicines, NAMENDA XR can cause side effects, although not everyone gets them.

Do not be alarmed by this list of possible side effects. You may not experience any of them.

The most common side effects in patients taking NAMENDA XR were headache, diarrhea and dizziness.

How to store NAMENDA XR:

Do not use NAMENDA XR after the expiration date shown on the carton and bottle.

Store at 25°C (77°F).

Do not use any capsules of NAMENDA XR that are damaged or show signs of tampering.

Keep NAMENDA XR out of the reach and sight of children and pets.

Manufactured for:Forest Pharmaceuticals, Inc. Subsidiary of Forest Laboratories, Inc. St. Louis, MO 63045

Manufactured by: Forest Laboratories Ireland Ltd

Licensed from Merz Pharmaceuticals GmbH